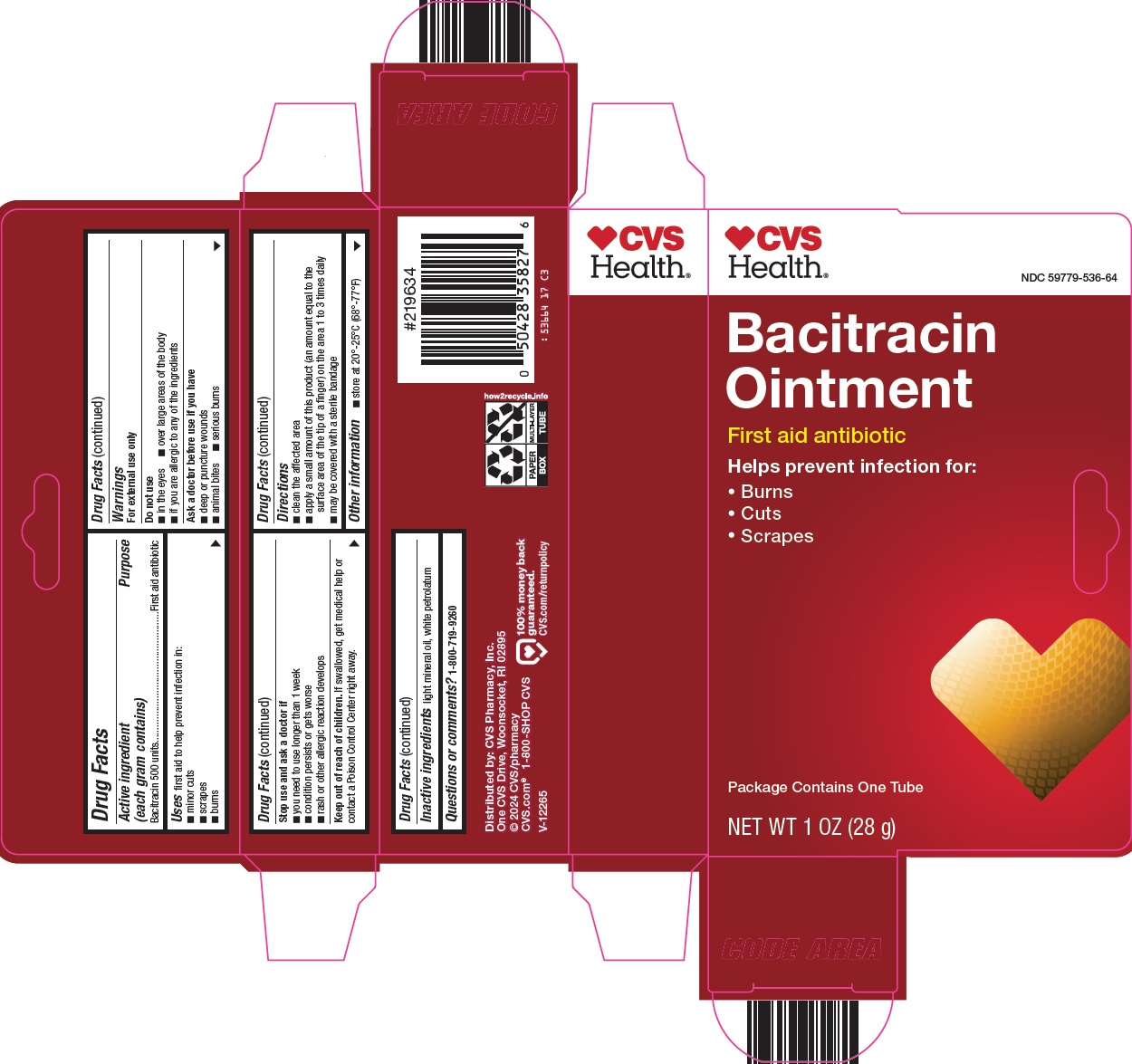 DRUG LABEL: BACITRACIN
NDC: 59779-536 | Form: OINTMENT
Manufacturer: CVS Pharmacy
Category: otc | Type: HUMAN OTC DRUG LABEL
Date: 20241022

ACTIVE INGREDIENTS: BACITRACIN 500 [USP'U]/1 g
INACTIVE INGREDIENTS: LIGHT MINERAL OIL; PETROLATUM

CVS Pharmacy, Inc. Bacitracin Ointment Drug Facts

Active ingredient (each gram contains)

Bacitracin 500 units

Purpose

First aid antibiotic

Uses

first aid to help prevent infection in:

1. minor cuts
2. scrapes
3. burns

Warnings

For external use only

Do not use

1. in the eyes
2. over large areas of the body
3. if you are allergic to any of the ingredients

Ask a doctor before use if you have

1. deep or puncture wounds
2. animal bites
3. serious burns

Stop use and ask a doctor if

1. you need to use longer than 1 week
2. condition persists or gets worse
3. rash or other allergic reaction develops

Keep out of reach of children.

If swallowed, get medical help or contact a Poison Control Center right away.

Directions

1. clean the affected area
2. apply a small amount of this product (an amount equal to the surface area of the tip of a finger) on the area 1 to 3 times daily
3. may be covered with a sterile bandage

Other information

1. store at 20°-25°C (68°-77°F)

Inactive ingredients

light mineral oil, white petrolatum

Questions or comments?

1-800-719-9260

Principal Display Panel

CVS Health®

Bacitracin Ointment

First aid antibiotic

Helps prevent infection for:

• Burns

• Cuts

• Scrapes

Package Contains One Tube

NET WT 1 OZ (28 g)